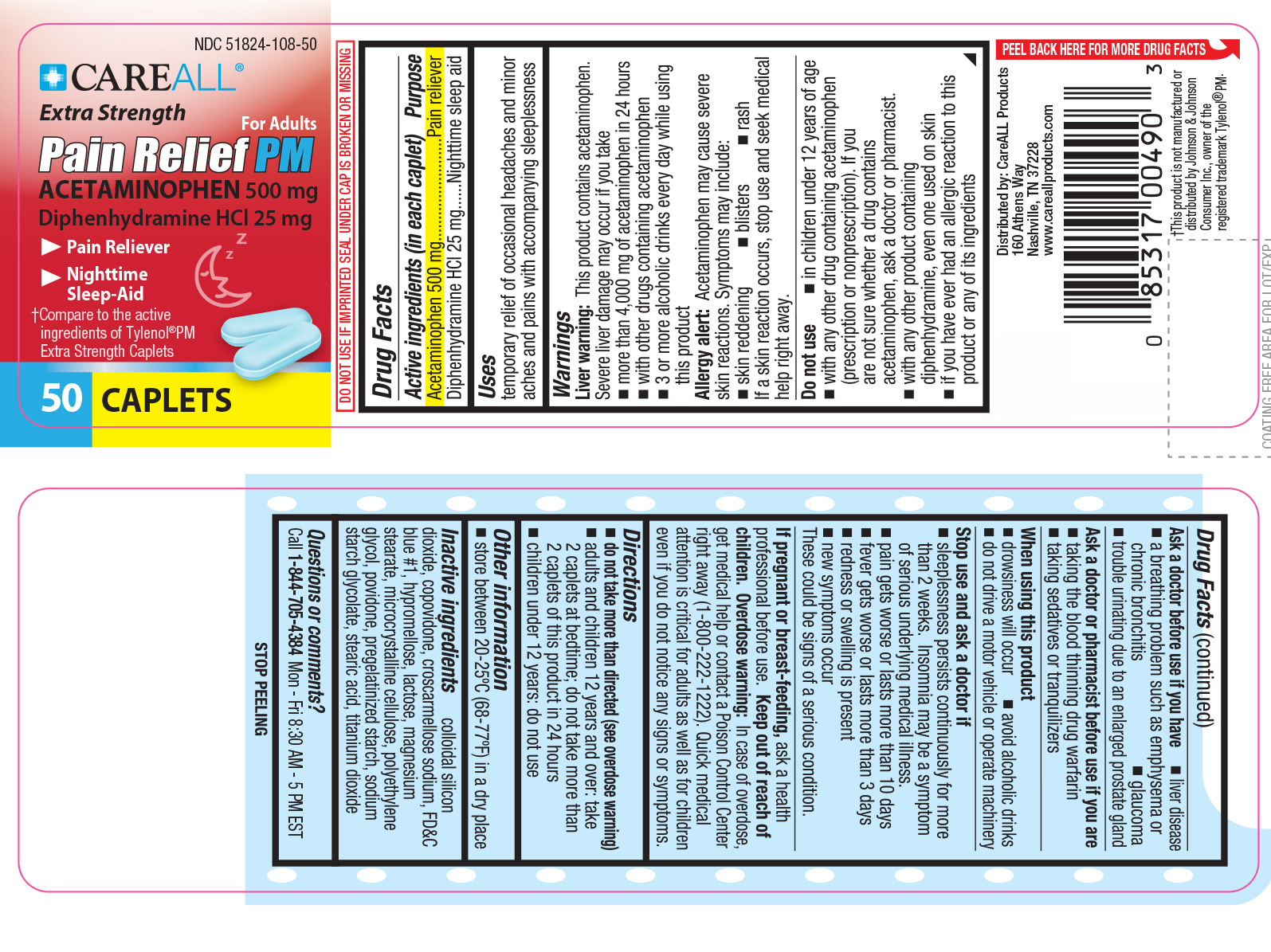 DRUG LABEL: CAREALL Pain Relief PM

NDC: 51824-108 | Form: TABLET
Manufacturer: New World Imports, Inc
Category: otc | Type: HUMAN OTC DRUG LABEL
Date: 20251222

ACTIVE INGREDIENTS: ACETAMINOPHEN 500 mg/1 1; DIPHENHYDRAMINE HYDROCHLORIDE 25 mg/1 1
INACTIVE INGREDIENTS: CROSCARMELLOSE SODIUM; FD&C BLUE NO. 1; HYPROMELLOSES; CELLULOSE, MICROCRYSTALLINE; POVIDONE; STARCH, CORN; STEARIC ACID; TITANIUM DIOXIDE; SILICON DIOXIDE; SODIUM STARCH GLYCOLATE TYPE A CORN; COPOVIDONE K25-31; LACTOSE, UNSPECIFIED FORM; MAGNESIUM STEARATE; POLYETHYLENE GLYCOL, UNSPECIFIED

Drug Facts

Active Ingredients

Acetaminophen 500mg

Diphenhydramine HCl 25mg

Purpose

Pain reliever

Nightime sleep aid

Keep out of reach of children.In case of accidental overdose, contact a doctor or Poison Control Center (1-800-222-1222) right away. Quick Medical attention is critical for adults as well as for children even if you do not notice any signs or symptoms.

Uses

Temporarily relieves occasional headaches and minor aches and pains with accompanying sleeplessness

Warnings

Liver Warning: This product contains Acetaminophen. Severe liver damage may occur if you take
• More than 4,000 mg of acetaminophen in 24 hours
• with other drugs containing acetaminophen
• 3 or more alcoholic drinks every day while using this product.

Allergy Alert:Acetaminophen may cause sever skin reactions. Symptoms may include: skin reddening, blisters, rash. If a skin reaction occurs, stop use and seek medical help right away.

Do not use:

- in children under 12 years of age
- with any other drug containing acetaminophen (prescription or nonprescription). If you are not sure whether a drug contains acetaminophen, ask a doctor or pharmacist.
- with any other product containing diphenhydramine, even one used on skin
- if you have even had an allergic reaction to this product or any of its ingredients

Ask a doctor before use if you have

- liver disease
- a breathing problem such as emphysema or chronic bronchitis
- trouble urinating due to an enlarged prostate gland
- glaucoma

Ask a doctor or pharmacist before use if you are

- taking the blood thinning drug warfarin
- taking sedatives or tranquilizers

When using this product

•drowsiness will occur

•do not drive a motor vehicle or operate machinery

•avoid alcoholic drinks

Stop use and ask a doctor if

•sleeplessness persists continuously for more than 2 weeks. Insomnia may be a symptom of serious underlying medical illness

•pain gets worse or last for more than 10 days.

•fever gets worse or last for more than 3 days

•redness or swelling are present

•new symptoms occur. These could be signs of a serious condition.

If pregnant or breast-feeding, ask a health professional before use.

Directions

Do not use more than directed. (see overdose warning)

Adults and children 12 years of age and older:Take 2 caplets at bedtime. Do not take more than 2 caplets in 24 hours

Children under 12 years:do not use

Inactive Ingredients

colloidal silicon dioxide, copovidone, croscarmellose sodium, FD and C blue 1, hypromellose, lactose, magnesium, stearate, microcrystalline cellulose, polyethylene glycol, povidone, pregelatinized starch, sodium starch glycolate, stearic acid, titanium dioxide